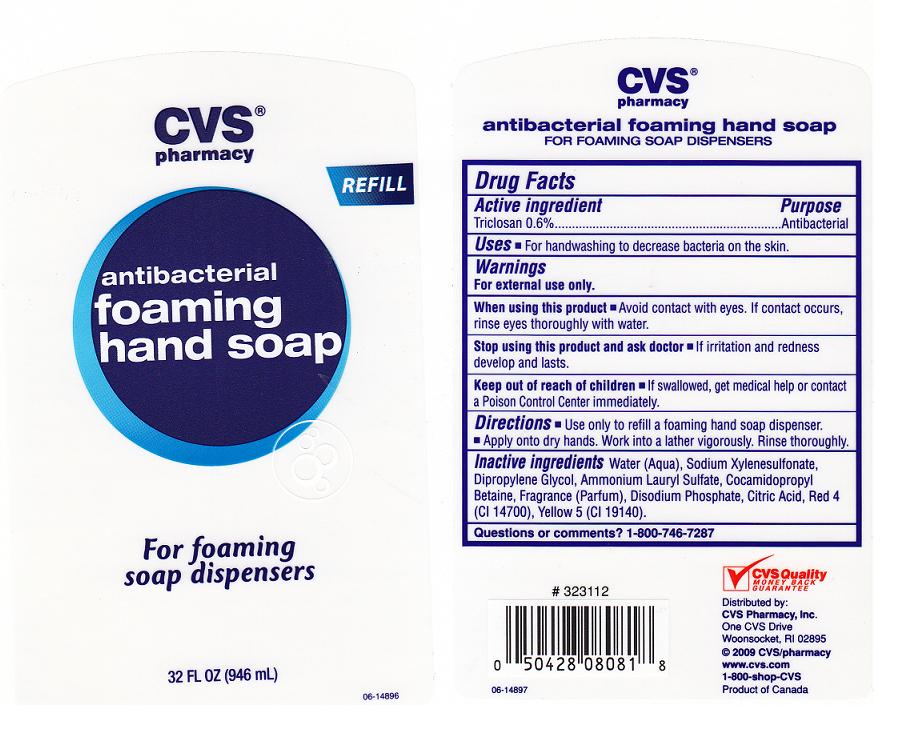 DRUG LABEL: ANTIBACTERIAL FOAMING
NDC: 59779-168 | Form: LIQUID
Manufacturer: CVS PHARMACY
Category: otc | Type: HUMAN OTC DRUG LABEL
Date: 20110518

ACTIVE INGREDIENTS: TRICLOSAN 0.6 mL/100 mL
INACTIVE INGREDIENTS: WATER; SODIUM XYLENESULFONATE; DIPROPYLENE GLYCOL; AMMONIUM LAURYL SULFATE; COCAMIDOPROPYL BETAINE; SODIUM PHOSPHATE, DIBASIC, DIHYDRATE; ANHYDROUS CITRIC ACID; FD&C RED NO. 4; FD&C YELLOW NO. 5

Drug Facts

ACTIVE INGREDIENT

TRICLOSAN 0.6 PERCENT

PURPOSE

ANTIBACTERIAL

USES

FOR HAND WASHING TO DECREASE BACTERIA ON THE SKIN.

WARNINGS

FOR EXTERNAL USE ONLY.

WHEN USING THIS PRODUCT

AVOID CONTACT WITH EYES. IF CONTACT OCCURS, RINSE THROUGHLY WITH WATER.

STOP USING THIS PRODUCT AND ASK DOCTOR

IF IRRITATION AND REDNESS DEVELOP AND LASTS.

KEEP OUR OF REACH OF CHILDREN

IF SWALLOWED, GET MEDICAL HELP OR CONTACT A POISON CONTROL CENTER IMMEDIATELY.

DIRECTIONS

USE ONLY TO REFILL A FOAMING HAND SOAP DISPENSER. APPLY ONTO DRY HANDS. WORK INTO A LATHER VIGOROUSLY. RINSE THOROUGHLY.

INACTIVE INGREDIENTS

WATER, SODIUM XYLENESULFONATE, DIPROPYLENE GLYCOL, AMMONIUM LAURYL SULFATE, COCAMIDOPROPYL BETAINE, FRAGRANCE, DISODIUM PHOSPHATE, CITRIC ACID, RED 4 (CI 14700),YELLOW 5 (CI 19140).